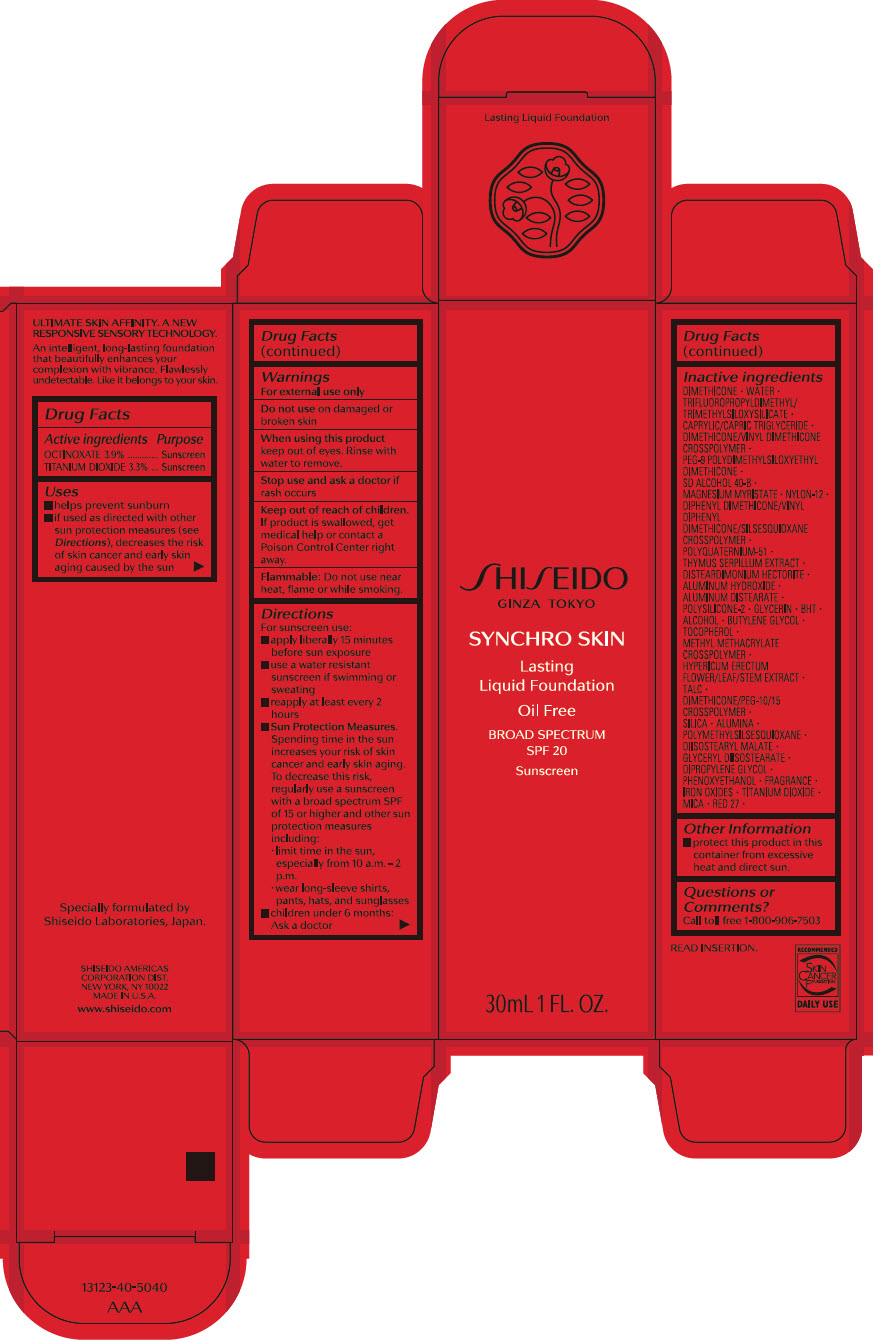 DRUG LABEL: SHISEIDO SYNCHRO SKIN LASTING Liquid FOUNDATION Neutral 5
NDC: 58411-624 | Form: EMULSION
Manufacturer: SHISEIDO AMERICAS CORPORATION
Category: otc | Type: HUMAN OTC DRUG LABEL
Date: 20260106

ACTIVE INGREDIENTS: OCTINOXATE 1.31 g/30 mL; TITANIUM DIOXIDE 1.09 g/30 mL
INACTIVE INGREDIENTS: DIMETHICONE; WATER; FERRIC OXIDE RED; FERRIC OXIDE YELLOW; FERROSOFERRIC OXIDE; MEDIUM-CHAIN TRIGLYCERIDES; DIMETHICONE/VINYL DIMETHICONE CROSSPOLYMER (SOFT PARTICLE); PEG-9 POLYDIMETHYLSILOXYETHYL DIMETHICONE; MAGNESIUM MYRISTATE; NYLON-12; DISTEARDIMONIUM HECTORITE; ALUMINUM HYDROXIDE; STEARIC ACID; GLYCERIN; BUTYLATED HYDROXYTOLUENE; ALCOHOL; BUTYLENE GLYCOL; .ALPHA.-TOCOPHEROL; METHYL METHACRYLATE/GLYCOL DIMETHACRYLATE CROSSPOLYMER; POLYQUATERNIUM-51 (2-METHACRYLOYLOXYETHYL PHOSPHORYLCHOLINE/N-BUTYL METHACRYLATE; 3:7); THYMUS SERPYLLUM WHOLE; PHENOXYETHANOL; HYPERICUM ERECTUM FLOWERING TOP; TALC; MICA; DIMETHICONE/PEG-10/15 CROSSPOLYMER; SILICON DIOXIDE; ALUMINUM OXIDE; POLYMETHYLSILSESQUIOXANE (4.5 MICRONS); D&C RED NO. 27; DIISOSTEARYL MALATE; GLYCERYL DIISOSTEARATE; DIPROPYLENE GLYCOL

SHISEIDO SYNCHRO SKIN LASTING LIQUID FOUNDATION

Drug Facts

ACTIVE INGREDIENT

Active ingredients | Purpose
OCTINOXATE 2.9 % | Sunscreen
TITANIUM DIOXIDE 2.4 % | Sunscreen

Uses

- helps prevent sunburn
- if used as directed with other sun protection measures (see Directions), decreases the risk of skin cancer and early skin aging caused by the sun

Warnings

For external use only

Do not use on damaged or broken skin

WHEN USING

When using this productkeep out of eyes. Rinse with water to remove.

Stop use and ask a doctorif rash occurs.

Keep out of reach of children.If product is swallowed, get medical help or contact a Poison Control Center right away.

Flammable;Do not use near heat, flam or white smoking.

Directions

For sunscreen use:

- apply liberally 15 minutes before sun exposure
- use a water resistant sunscreen if swimming or sweating
- reapply at least every two hours
- Sun Protection Measures. Spending time in the sun increases your risk of skin cancer and early skin aging. To decrease this risk, regularly use a sunscreen with a broad spectrum SPF of 15 or higher and other sun protection measures including:
  - limit time in the sun, especially from 10 a.m. – 2 p.m.
  - wear long-sleeve shirts, pants, hats, and sunglasses
  - children under 6 months: Ask a doctor

Inactive Ingredients

DIMETHICONE∙WATER∙TRIFLUOROPROPYLDIMETHYL/TRIMETHYLSILOXYSILICATE∙CAPRYLIC/CAPRIC TRIGLYCERIDE∙DIMETHICONE/VINYL DIMETHICONE CROSSPOLYMER∙PEG-9 POLYDIMETHYLSILOXYETHYL DIMETHICONE∙SD ALCOHOL 40-B∙MAGNESIUM MYRISTATE∙NYLON-12∙DIPHENYL DIMETHICONE/VINYL DIPHENYL DIMETHICONE/SILSESQUIOXANE CROSSPOLYMER∙DISTEARDIMONIUM HECTORITE∙POLYQUATERNIUM-51∙THYMUS SERPILLUM EXTRACT∙ALUMINUM HYDROXIDE∙ALUMINUM DISTEARATE∙POLYSILICONE-2∙GLYCERIN∙BHT∙ALCOHOL∙BUTYLENE GLYCOL∙TOCOPHEROL∙METHYL METHACRYLATE CROSSPOLYMER∙HYPERICUM ERECTUM FLOWER/LEAF/STEM EXTRACT∙TALC∙DIMETHICONE/PEG-10/15 CROSSPOLYMER∙SILICA∙ALUMINA∙POLYMETHYLSILSESQUIOXANE∙DIISOSTEARYL MALATE∙GLYCERYL DIISOSTEARATE∙DIPROPYLENE GLYCOL∙PHENOXYETHANOL∙FRAGRANCE∙TITANIUM DIOXIDE∙IRON OXIDES∙MICA∙RED 27∙

Other information

Protect this product in this container from excessive heat and direct sun.

Questions or comments?

Call toll free 1-800-906-7503

PRINCIPAL DISPLAY PANEL - 30 mL Bottle Carton - Neutral 5

SHISEIDO
GINZA TOKYO

SYNCHRO SKIN

Lasting
Liquid Foundation

Oil Free

BROAD SPECTRUM
SPF 20

Sunscreen

30mL 1 FL. OZ.

PRINCIPAL DISPLAY PANEL - 30 mL Bottle Carton - Rose 5

SHISEIDO
GINZA TOKYO

SYNCHRO SKIN

Lasting
Liquid Foundation

Oil Free

BROAD SPECTRUM
SPF 20

Sunscreen

30mL 1 FL. OZ.

PRINCIPAL DISPLAY PANEL - 30 mL Bottle Carton - Golden 5

SHISEIDO
GINZA TOKYO

SYNCHRO SKIN

Lasting
Liquid Foundation

Oil Free

BROAD SPECTRUM
SPF 20

Sunscreen

30mL 1 FL. OZ.